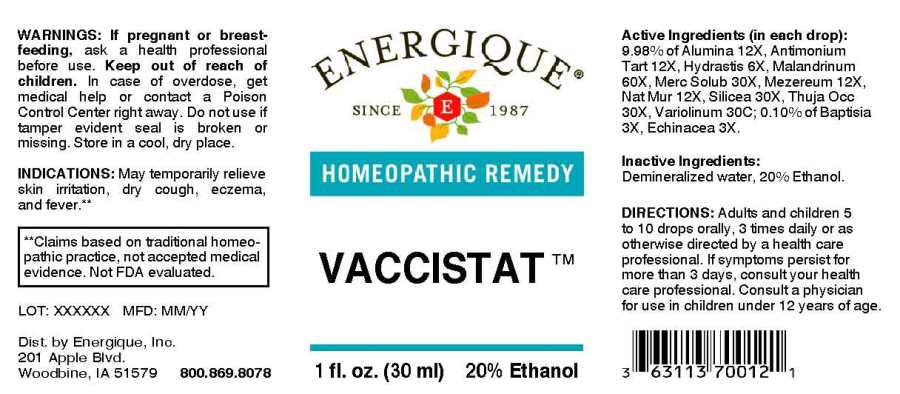 DRUG LABEL: Vaccistat
NDC: 44911-0633 | Form: LIQUID
Manufacturer: Energique, Inc.
Category: homeopathic | Type: HUMAN OTC DRUG LABEL
Date: 20241031

ACTIVE INGREDIENTS: BAPTISIA TINCTORIA ROOT 3 [hp_X]/1 mL; ECHINACEA ANGUSTIFOLIA WHOLE 3 [hp_X]/1 mL; GOLDENSEAL 6 [hp_X]/1 mL; ALUMINUM OXIDE 12 [hp_X]/1 mL; ANTIMONY POTASSIUM TARTRATE 12 [hp_X]/1 mL; DAPHNE MEZEREUM BARK 12 [hp_X]/1 mL; SODIUM CHLORIDE 12 [hp_X]/1 mL; MERCURIUS SOLUBILIS 30 [hp_X]/1 mL; SILICON DIOXIDE 30 [hp_X]/1 mL; THUJA OCCIDENTALIS LEAFY TWIG 30 [hp_X]/1 mL; VACCINIA VIRUS 60 [hp_X]/1 mL; VACCINIA VIRUS STRAIN NEW YORK CITY BOARD OF HEALTH LIVE ANTIGEN 30 [hp_C]/1 mL
INACTIVE INGREDIENTS: WATER; ALCOHOL

DRUG FACTS:

ACTIVE INGREDIENTS:

(in each drop): 9.98% of Alumina 12X, Antimonium Tartaricum 12X, Hydrastis Canadensis 6X, Malandrinum 60X, Mercurius Solubilis 30X, Mezereum 12X, Natrum Muriaticum 12X, Silicea 30X, Thuja Occidentalis 30X, Variolinum 30C; 0.10% of Baptisia Tinctoria 3X, Echinacea (Angustifolia) 3X.

INDICATIONS:

May temporarily relieve skin irritation, dry cough, eczema, and fever.**

**Claims based on traditional homeopathic practice, not accepted medical evidence. Not FDA evaluated.

WARNINGS:

If pregnant or breast-feeding, ask a health professional before use.
Keep out of reach of children. In case of overdose, get medical help or contact a Poison Control Center right away.
Do not use if tamper evident seal is broken or missing. Store in a cool, dry place.

Keep out of reach of children. In case of overdose, get medical help or contact a Poison Control Center right away.

DIRECTIONS:

Adults and children 5 to 10 drops orally, 3 time daily or as otherwise directed by a health care professional. If symptoms persist for more than 3 days, consult your health care professional.
Consult a physician for use in children under 12 years of age.

INDICATIONS:

May temporarily relieve skin irritation, dry cough, eczema, and fever.**

**Claims based on traditional homeopathic practice, not accepted medical evidence. Not FDA evaluated.

INACTIVE INGREDIENTS:

Demineralized water, 20% Ethanol.

QUESTIONS:

Dist. by Energique, Inc.
201 Apple Blvd
Woodbine, IA 51579 800.869.8078

PACKAGE LABEL DISPLAY:

ENERGIQUE
SINCE 1987
HOMEOPATHIC REMEDY
VACCISTAT
1 fl. oz. (30 ml)